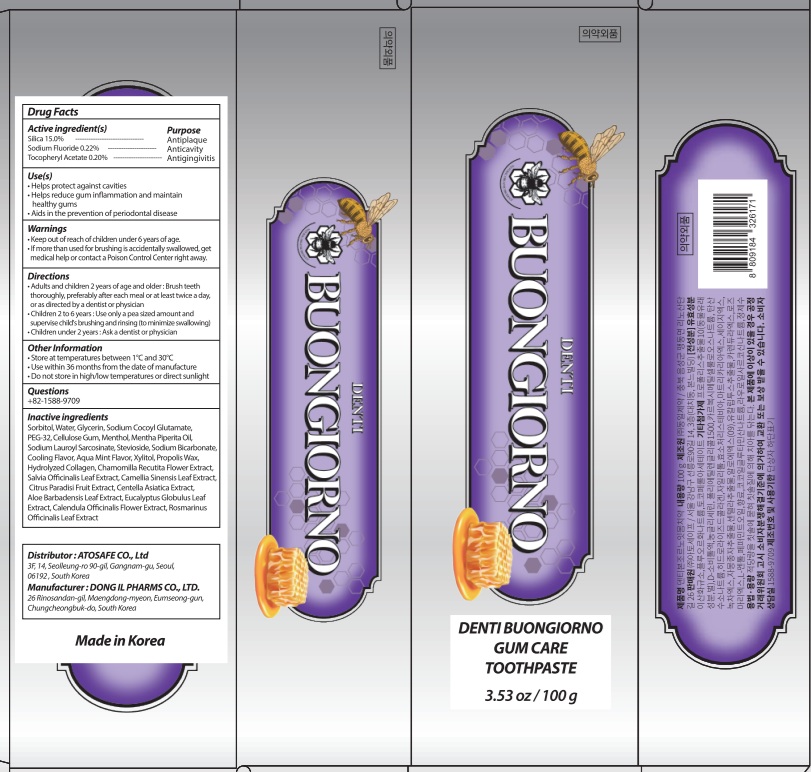 DRUG LABEL: DENTI BUONGIORNO GUM CARE TOOTH
NDC: 85601-070 | Form: PASTE, DENTIFRICE
Manufacturer: ATOSAFE CO., Ltd
Category: otc | Type: HUMAN OTC DRUG LABEL
Date: 20251013

ACTIVE INGREDIENTS: .ALPHA.-TOCOPHEROL ACETATE 0.2 g/100 g; SILICON DIOXIDE 15 g/100 g; SODIUM FLUORIDE 0.22 g/100 g
INACTIVE INGREDIENTS: SODIUM COCOYL GLUTAMATE; SORBITOL; WATER; GLYCERIN

Active ingredient(s)

Silica 17.0%

Sodium Fluoride 0.22%

Tocopheryl Acetate 0.20%

Purpose

Antiplaque, Anticavity, Antigingivitis

Warnings

• Keep out of reach of children under 6 years of age.
• If more than used for brushing is accidentally swallowed, get medical help or contact a Poison Control Center right away.

KEEP OUT OF REACH OF CHILDREN

Keep out of reach of childrenunder 6 years of age.

INDICATIONS AND USAGE

Use(s)

• Helps protect against cavities
• Helps reduce gum inflammation and maintain healthy gums
• Aids in the prevention of periodontal disease

Directions

• Adults and children 2 years of age and older: Brush teeth thoroughly, preferably after each meal or at least twice a day, or as directed by a dentist or physician
• Children 2 to 6 years: Use only a pea-sized amount and supervise brushing and rinsing (to minimize swallowing).
• Children under 2 years: Ask a dentist or physician.

Other Information

• Store at temperatures between 1°C and 30°C
• Use within 36 months from the date of manufacture
• Do not store in high/low temperatures or direct sunlight

Questions

+82-1588-9709

Inactive ingredients

Sorbitol, Water, Glycerin, Sodium Cocoyl Glutamate, PEG-32, Cellulose Gum, Menthol, Mentha Piperita Oil, Sodium Lauroyl Sarcosinate, Stevioside, Sodium Bicarbonate, Cooling Flavor, Aqua Mint Flavor, Xylitol, Propolis Wax, Hydrolyzed Collagen, Chamomilla Recutita Flower Extract, Salvia Officinalis Leaf Extract, Camellia Sinensis Leaf Extract, Citrus Paradisi Fruit Extract, Centella Asiatica Extract, Aloe Barbadensis Leaf Extract, Eucalyptus Globulus Leaf Extract, Calendula Officinalis Flower Extract, Rosmarinus Officinalis Leaf Extract